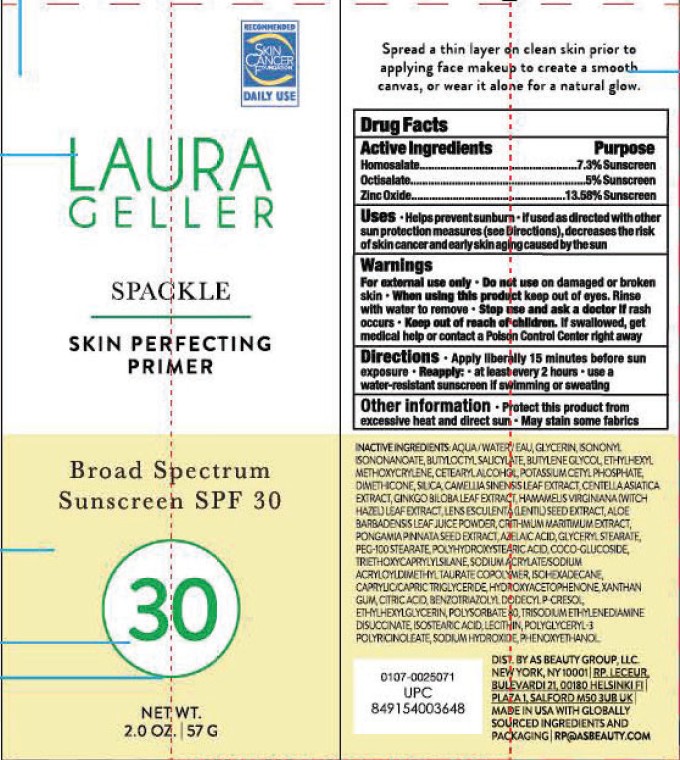 DRUG LABEL: Laura Geller Spackle Skin Perfecting Primer Broad Spectrum SPF 30 Sunscreen
NDC: 74884-893 | Form: CREAM
Manufacturer: AS BEAUTY
Category: otc | Type: HUMAN OTC DRUG LABEL
Date: 20250506

ACTIVE INGREDIENTS: OCTISALATE 50 mg/1 g; HOMOSALATE 73 mg/1 g; ZINC OXIDE 136.8 mg/1 g
INACTIVE INGREDIENTS: BUTYLOCTYL SALICYLATE; POLYHYDROXYSTEARIC ACID (2300 MW); BUTYLENE GLYCOL; GLYCERYL STEARATE; TRIETHOXYCAPRYLYLSILANE; XANTHAN GUM; GLYCERIN; DIMETHICONE; POLYSORBATE 80; ISOHEXADECANE; ETHYLHEXYLGLYCERIN; SODIUM HYDROXIDE; ISOSTEARIC ACID; CETEARYL ALCOHOL; COCO-GLUCOSIDE; HYDROXYACETOPHENONE; BENZOTRIAZOLYL DODECYL P-CRESOL; PHENOXYETHANOL; SODIUM ACRYLATE/SODIUM ACRYLOYLDIMETHYLTAURATE COPOLYMER (4000000 MW); WATER; ISONONYL ISONONANOATE; ETHYLHEXYL METHOXYCRYLENE; POTASSIUM CETYL PHOSPHATE; PEG-100 STEARATE; CITRIC ACID; TRISODIUM ETHYLENEDIAMINE DISUCCINATE; CAPRYLIC/CAPRIC TRIGLYCERIDE

Active Ingredients

Homosalate...............7.3%

Octisalate.............5%

Zinc Oxide.............13.68%

Purpose

..........Sunscreen

Uses

- Helps prevents sunburn
- If used as directed with other sun protection measures (see Direction), decreases the risk of skin cancer and early skin aging caused by the sun

Warnings

For external use only

Do not use on damaged or broken skin

Do not use on damaged or broken skin

When using this product keep out of eyes. Rinse with water to remove.

Stop use and ask a doctor if rash occurs

Keep out of reach of children. If swallowed, get medical help or contact a Poison Control Center right away.

DIrections

- Apply liberally 15 minutes before sun exposure
- Reapply at least every 2 hours use a water-resistant sunscreen if swimming or sweating

Other information

- Protect this product form excessive heat and direct sun
- May stain some fabrics

INACTIVE INGREDIENT

INACTIVE INGREDIENTS: AQUA/WATER/EAU, GLYCERIN, ISONONUL ISONONANOATE, BUTYLOCTYL SALICYLATE, BUTYLENE GLYCOL, ETHYLHEXYL METHOXYCRYLENE, CETEARYL ALCOHOL, POTASSIUM CETYL PHOSPHATE, DIMETHICONE, SILICA, CAMELLIA SINENSIS LEAF EXTRACT, CENTELLA ASIATICA EXTRACT, GINKGO BILOBA LEAF EXTRACT, HAMAMELIS VIRGINIANA (WITCH HAZEL) LEAF EXTRACT, LENS ESCULENTA (LENTIL) SEED EXTRACT, ALOE BARBADENSIS LEAF JUICE POWDER, CRITHMUM MARITIMUM EXTRACT, PONGAMIA PINNATA SEED EXTRACT, AZELAIC ACID, GLYCERYL STEARATE, PEG-100 STEARATE, POLYHYDROXYSTEARIC ACID, COCO-GLUCOSIDE, TRIETHOXYCAPRYLYLSILANE, SODIUM ACRYLATE/SODIUM ACRYLOYLDIMETHYL TAURATE COPOLYMER, ISOHEXADECANE, CAPRYLIC/CAPRIC TRIGLYCERIDE, HYDROXYACETOPHENONE, XANTHAN GUM, CITRIC ACID, BENZOTRIAZOLYL DODECYL P-CRESOL, ETHYLHEXYLGLYCERIN, POLYSORBATE 80, TRISODIUM ETHYLENEDIAMINE DISUCCINATE, ISOSTEARIC ACID, LECITHIN, POLYGLYCERYL-3 POLYRICINOLEATE, SODIUM HYDROXIDE, PHENOXYETHANOL